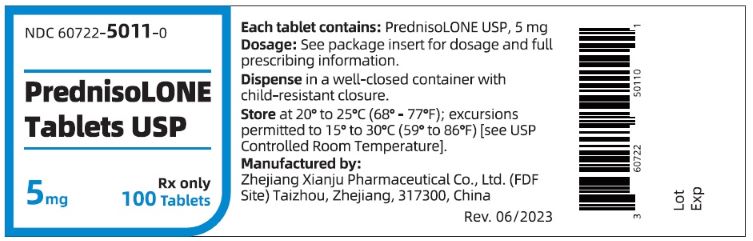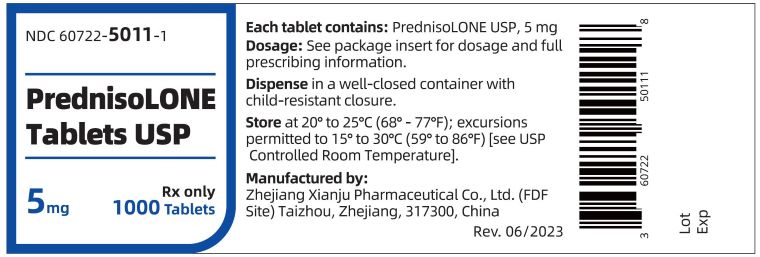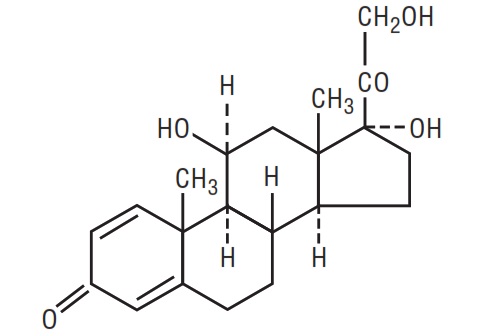 DRUG LABEL: PREDNISOLONE
NDC: 60722-5011 | Form: TABLET
Manufacturer: Zhejiang Xianju Pharmaceutical Co., Ltd.
Category: prescription | Type: HUMAN PRESCRIPTION DRUG LABEL
Date: 20260105

ACTIVE INGREDIENTS: PREDNISOLONE 5  mg/1 1
INACTIVE INGREDIENTS: ANHYDROUS LACTOSE; SILICON DIOXIDE; CROSPOVIDONE; DOCUSATE SODIUM; D&C YELLOW NO. 10; FD&C YELLOW NO. 6; MAGNESIUM STEARATE; SODIUM BENZOATE

PREDNISOLONE TABLETS, USP
Rx only

DESCRIPTION

Glucocorticoids are adrenocortical steroids, both naturally occurring and synthetic, which are readily absorbed from the gastrointestinal tract. Prednisolone is a white crystalline powder, very slightly soluble in water. It is designated chemically as pregna-1,4-diene-3,20-dione,11,17,21-trihydroxy-, (11ß)-. The structural formula is represented below:

C21 H28 O5 M.W. 360.45

Prednisolone Tablets, USP, 5 mg contain the following inactive ingredients: anhydrous lactose, colloidal silicon dioxide, crospovidone, D&C Yellow No. 10, docusate sodium, FD&C Yellow No. 6, magnesium stearate and sodium benzoate.

FDA approved dissolution test specifications differ from USP.

CLINICAL PHARMACOLOGY

Naturally occurring glucocorticoids (hydrocortisone and cortisone), which also have salt-retaining properties, are used as replacement therapy in adrenocortical deficiency states. Prednisolone is primarily used for its potent anti-inflammatory effects in disorders of many organ systems.

Glucocorticoids cause profound and varied metabolic effects. In addition, they modify the body's immune responses to diverse stimuli.

INDICATIONS AND USAGE

1. Endocrine disorders. Primary or secondary adrenocortical insufficiency (hydrocortisone or cortisone is the first choice; synthetic analogs may be used in conjunction with mineralocorticoids where applicable; in infancy mineralocorticoid supplementation is of particular importance).

Congenital adrenal hyperplasia

Nonsuppurative thyroiditis

Hypercalcemia associated with cancer

2. Rheumatic disorders. As adjunctive therapy for short-term administration (to tide the patient over an acute episode or exacerbation) in:

Psoriatic arthritis

Rheumatoid arthritis; including juvenile rheumatoid arthritis (selected cases may require low-dose maintenance therapy)

Ankylosing spondylitis

Acute and subacute bursitis

Acute nonspecific tenosynovitis

Acute gouty arthritis

Post-traumatic osteoarthritis

Synovitis of osteoarthritis

Epicondylitis

3. Collagen diseases. During an exacerbation or as maintenance therapy in selected cases of:

Systemic lupus erythematosus

Acute rheumatic carditis

Systemic dermatomyositis (polymyositis)

4. Dermatologic diseases

Pemphigus

Bullous dermatitis herpetiformis

Severe erythema multiforme (Stevens-Johnson syndrome)

Exfoliative dermatitis

Mycosis fungoides

Severe psoriasis

Severe seborrheic dermatitis

5. Allergic states. Control of severe or incapacitating allergic conditions intractable to adequate trials of conventional treatment:

Seasonal or perennial allergic rhinitis

Serum sickness

Bronchial asthma

Contact dermatitis

Atopic dermatitis

Drug hypersensitivity reactions

6. Ophthalmic diseases. Severe acute and chronic allergic and inflammatory processes involving the eye and its adnexa such as:

Allergic conjunctivitis

Keratitis

Allergic corneal marginal ulcers

Herpes zoster ophthalmicus

Iritis and iridocyclitis

Chorioretinitis

Anterior segment inflammation

Diffuse posterior uveitis and choroiditis

Optic neuritis

Sympathetic ophthalmia

7. Respiratory diseases

Symptomatic sarcoidosis

Loeffler's syndrome not manageable by other means

Berylliosis

Fulminating or disseminated pulmonary tuberculosis when used concurrently with appropriate antituberculous chemotherapy

Aspiration pneumonitis

8. Hematologic disorders

Idiopathic thrombocytopenic purpura in adults

Secondary thrombocytopenia in adults

Acquired (autoimmune) hemolytic anemia

Erythroblastopenia (RBC anemia)

Congenital (erythroid) hypoplastic anemia

9. Neoplastic diseases. For palliative management of:

Leukemias and lymphomas in adults

Acute leukemia of childhood

10. Edematous states. To induce a diuresis or remission of proteinuria in the nephrotic syndrome, without uremia, of the idiopathic type or that due to lupus erythematosus.

11. Gastrointestinal diseases. To tide the patient over a critical period of the disease in:

Ulcerative colitis

Regional enteritis

12. Nervous system. Acute exacerbations of multiple sclerosis

13. Miscellaneous

Tuberculous meningitis with subarachnoid block or impending block when used concurrently with appropriate antituberculous chemotherapy

Trichinosis with neurologic or myocardial involvement

CONTRAINDICATIONS

Systemic fungal infections

WARNINGS

Persons who are on drugs which suppress the immune system are more susceptible to infections than healthy individuals. Chickenpox and measles, for example, can have a more serious or even fatal course in non-immune children or adults on corticosteroids. In such children or adults who have not had these diseases, particular care should be taken to avoid exposure. How the dose, route and duration of corticosteroid administration affects the risk of developing a disseminated infection is not known. The contribution of the underlying disease and/or prior corticosteroid treatment to the risk is also not known. If exposed to chickenpox, prophylaxis with varicella zoster immune globulin (VZIG) may be indicated. If exposed to measles, prophylaxis with pooled intramuscular immunoglobulin (IG) may be indicated. (See the respective package inserts for complete VZIG and IG prescribing information.) If chickenpox develops, treatment with antiviral agents may be considered.

In patients on corticosteroid therapy subjected to unusual stress increased dosage of rapidly acting corticosteroids before, during, and after the stressful situation is indicated.

Corticosteroids may mask some signs of infection, and new infections may appear during their use. There may be decreased resistance and inability to localize infection when corticosteroids are used.

Prolonged use of corticosteroids may produce posterior subcapsular cataracts, glaucoma with possible damage to the optic nerves, and may enhance the establishment of secondary ocular infections due to fungi or viruses.

Usage in Pregnancy

Since adequate human reproduction studies have not been done with corticosteroids, the use of these drugs in pregnancy, nursing mothers or women of childbearing potential requires that the possible benefits of the drug be weighed against the potential hazards to the mother and embryo or fetus. Infants born of mothers who have received substantial doses of corticosteroids during pregnancy, should be carefully observed for signs of hypoadrenalism.

Average and large doses of hydrocortisone or cortisone can cause elevation of blood pressure, salt and water retention, and increased excretion of potassium. These effects are less likely to occur with synthetic derivatives except when used in large doses. Dietary salt restriction and potassium supplementation may be necessary. All corticosteroids increase calcium excretion.

While on corticosteroid therapy patients should not be vaccinated against smallpox. Other immunization procedures should not be undertaken in patients who are on corticosteroids, especially on high dose, because of possible hazards of neurological complications and a lack of antibody response.

The use of prednisolone in active tuberculosis should be restricted to those cases of fulminating or disseminated tuberculosis in which the corticosteroid is used for the management of the disease in conjunction with an appropriate antituberculous regimen.

If corticosteroids are indicated in patients with latent tuberculosis or tuberculin reactivity, close observation is necessary as reactivation of the disease may occur. During prolonged corticosteroid therapy, these patients should receive chemoprophylaxis.

PRECAUTIONS

Information for Patients

Persons who are on immunosuppressant doses of corticosteroids should be warned to avoid exposure to chickenpox or measles. Patients should also be advised that if they are exposed, medical advice should be sought without delay.

Drug-induced secondary adrenocortical insufficiency may be minimized by gradual reduction of dosage. This type of relative insufficiency may persist for months after discontinuation of therapy; therefore, in any situation of stress occurring during that period, hormone therapy should be reinstituted. Since mineralocorticoid secretion may be impaired, salt and/or a mineralocorticoid should be administered concurrently.

There is an enhanced effect of corticosteroids on patients with hypothyroidism and in those with cirrhosis.

Corticosteroids should be used cautiously in patients with ocular herpes simplex because of possible corneal perforation.

The lowest possible dose of corticosteroid should be used to control the condition under treatment, and when reduction in dosage is possible, the reduction should be gradual.

Psychic derangements may appear when corticosteroids are used, ranging from euphoria, insomnia, mood swings, personality changes, and severe depression, to frank psychotic manifestations. Also, existing emotional instability or psychotic tendencies may be aggravated by corticosteroids.

Aspirin should be used cautiously in conjunction with corticosteroids in hypoprothrombinemia.

Steroids should be used with caution in nonspecific ulcerative colitis, if there is a probability of impending perforation, abscess or other pyogenic infection; diverticulitis; fresh intestinal anastomoses; active or latent peptic ulcer; renal insufficiency; hypertension; osteoporosis and myasthenia gravis.

Growth and development of infants and children on prolonged corticosteroid therapy should be carefully observed.

Although controlled clinical trials have shown corticosteroids to be effective in speeding the resolution of acute exacerbations of multiple sclerosis they do not show that they affect the ultimate outcome or natural history of the disease. The studies do show that relatively high doses of corticosteroids are necessary to demonstrate a significant effect. (See DOSAGE AND ADMINISTRATION section.)

Since complications of treatment with glucocorticoids are dependent on the size of the dose and the duration of treatment, a risk/benefit decision must be made in each individual case as to dose and duration of treatment and as to whether daily or intermittent therapy should be used.

ADVERSE REACTIONS

Fluid and Electrolyte Disturbances

Sodium retention. Fluid retention. Congestive heart failure in susceptible patients. Potassium loss. Hypokalemic alkalosis.

Hypertension.

Musculoskeletal

Muscle weakness. Steroid myopathy. Loss of muscle mass. Osteoporosis. Vertebral compression fractures. Aseptic necrosis of femoral and humeral heads. Pathologic fracture of long bones.

Gastrointestinal

Peptic ulcer with possible perforation and hemorrhage. Pancreatitis. Abdominal distention. Ulcerative esophagitis.

Dermatologic

Impaired wound healing. Thin fragile skin. Petechiae and ecchymoses. Facial erythema. Increased sweating. May suppress reactions to skin tests.

Neurological

Convulsions. Increased intracranial pressure with papilledema (pseudotumor cerebri) usually after treatment. Vertigo. Headache.

Endocrine

Menstrual irregularities. Development of Cushingoid state. Suppression of growth in children. Secondary adrenocortical and pituitary unresponsiveness, particularly in times of stress, as in trauma, surgery, or illness. Decreased carbohydrate tolerance. Manifestations of latent diabetes mellitus. Increased requirements for insulin or oral hypoglycemic agents in diabetics.

Ophthalmic

Posterior subcapsular cataracts. Increased intraocular pressure. Glaucoma. Exophthalmos.

Metabolic

Negative nitrogen balance due to protein catabolism.

To report SUSPECTED ADVERSE REACTIONS, contact Zhejiang Xianju Pharmaceutical Co., Ltd. at 1-800-513-1761 or FDA at 1-800-FDA-1088 or www.fda.gov/medwatch.

DOSAGE AND ADMINISTRATION

The initial dosage of prednisolone tablets may vary from 5 mg to 60 mg per day depending on the specific disease entity being treated. In situations of less severity, lower doses will generally suffice, while in selected patients higher initial doses may be required. The initial dosage should be maintained or adjusted until a satisfactory response is noted. If after a reasonable period of time there is a lack of satisfactory clinical response, prednisolone should be discontinued and the patient transferred to other appropriate therapy.

IT SHOULD BE EMPHASIZED THAT DOSAGE REQUIREMENTS ARE VARIABLE AND MUST BE INDIVIDUALIZED ON THE BASIS OF THE DISEASE UNDER TREATMENT AND THE RESPONSE OF THE PATIENT.

After a favorable response is noted, the proper maintenance dosage should be determined by decreasing the initial drug dosage in small increments at appropriate time intervals until the lowest dosage which will maintain an adequate clinical response is reached. It should be kept in mind that constant monitoring is needed in regard to drug dosage. Included in the situations which may make dosage adjustments necessary are changes in clinical status secondary to remissions or exacerbations in the disease process, the patient's individual drug responsiveness, and the effect of patient exposure to stressful situations not directly related to the disease entity under treatment; in this latter situation it may be necessary to increase the dosage of prednisolone for a period of time consistent with the patient's condition. If after long-term therapy the drug is to be stopped, it is recommended that it be withdrawn gradually rather than abruptly.

Alternate-Day Therapy is a corticosteroid dosing regimen in which twice the usual daily dose of corticoid is administered every other morning. The purpose of this mode of therapy is to provide the patient requiring long-term pharmacologic dose treatment with the beneficial effects of corticoids while minimizing certain undesirable effects, including pituitary-adrenal suppression, the Cushingoid state, corticoid withdrawal symptoms, and growth suppression in children.

The rationale for this treatment schedule is based on two major premises: (a) the anti-inflammatory or therapeutic effect of corticoids persists longer than their physical presence and metabolic effects and (b) administration of the corticosteroid every other morning allows for re-establishment of more nearly normal hypothalamic-pituitary-adrenal (HPA) activity on the off-steroid day.

A brief review of the HPA physiology may be helpful in understanding this rationale. Acting primarily through the hypothalamus a fall in free cortisol stimulates the pituitary gland to produce increasing amounts of corticotropin (ACTH) while a rise in free cortisol inhibits ACTH secretion. Normally the HPA system is characterized by diurnal (circadian) rhythm. Serum levels of ACTH rise from a low point about 10 p.m. to a peak level about 6 a.m. Increasing levels of ACTH stimulate adrenocortical activity resulting in a rise in plasma cortisol with maximal levels occurring between 2 a.m. and 8 a.m. This rise in cortisol dampens ACTH production and in turn adrenocortical activity. There is a gradual fall in plasma corticoids during the day, the lowest levels occurring about midnight.

The diurnal rhythm of the HPA axis is lost in Cushing's disease, a syndrome of adrenocortical hyperfunction characterized by obesity with centripetal fat distribution, thinning of the skin with easy bruisability, muscle wasting with weakness, hypertension, latent diabetes, osteoporosis, electrolyte imbalance, etc. The same clinical findings of hyperadrenocorticism may be noted during the longterm pharmacologic dose corticoid therapy administered in conventional daily divided doses. It would appear, then, that a disturbance in the diurnal cycle with maintenance of elevated corticoid values during the night may play a significant role in the development of undesirable corticoid effects. Escape from these constantly elevated plasma levels for even short periods of time may be instrumental in protecting against undesirable pharmacologic effects.

During conventional pharmacologic dose corticosteroid therapy, ACTH production is inhibited with subsequent suppression of cortisol production by the adrenal cortex. Recovery time for normal HPA activity is variable depending upon the dose and duration of treatment. During this time the patient is vulnerable to any stressful situation. Although it has been shown that there is considerably less adrenal suppression following a single morning dose of prednisolone (10 mg) as opposed to a quarter of that dose administered every 6 hours, there is evidence that some suppressive effect on adrenal activity may be carried over into the following day when pharmacologic doses are used. Further, it has been shown that a single dose of certain corticosteroids will produce adrenocortical suppression for two or more days. Other corticoids, including methylprednisolone, hydrocortisone, prednisone, and prednisolone, are considered to be short acting (producing adrenocortical suppression for 1 1/4 days to 1 1/2 days following a single dose) and thus are recommended for alternate-day therapy.

The following should be kept in mind when considering alternate-day therapy:

1. Basic principles and indications for corticosteroid therapy should apply. The benefits of alternate-day therapy should not encourage the indiscriminate use of steroids.
2. Alternate-day therapy is a therapeutic technique primarily designed for patients in whom long-term pharmacologic corticoid therapy is anticipated.
3. In less severe disease processes in which corticoid therapy is indicated, it may be possible to initiate treatment with alternate-day therapy. More severe disease states usually will require daily divided high dose therapy for initial control of the disease process. The initial suppressive dose level should be continued until satisfactory clinical response is obtained, usually four to ten days in the case of many allergic and collagen diseases. It is important to keep the period of initial suppressive dose as brief as possible particularly when subsequent use of alternate-day therapy is intended.
  Once control has been established, two courses are available: (a) change to alternate-day therapy and then gradually reduce the amount of corticoid given every other day, or (b) following control of the disease process, reduce the daily dose of corticoid to the lowest effective level as rapidly as possible and then change over to an alternate-day schedule. Theoretically, course (a) may be preferable.
4. Because of the advantages of alternate-day therapy, it may be desirable to try patients on this form of therapy who have been on daily corticoids for long periods of time (e.g., patients with rheumatoid arthritis). Since these patients may already have a suppressed HPA axis, establishing them on alternate-day therapy may be difficult and not always successful. However, it is recommended that regular attempts be made to change them over. It may be helpful to triple or even quadruple the daily maintenance dose and administer this every other day rather than just doubling the daily dose if difficulty is encountered. Once the patient is again controlled, an attempt should be made to reduce this dose to a minimum.
5. As indicated above, certain corticosteroids, because of their prolonged suppressive effect on adrenal activity, are not recommended for alternate-day therapy (e.g., dexamethasone and betamethasone).
6. The maximal activity of the adrenal cortex is between 2 a.m. and 8 a.m., and it is minimal between 4 p.m. and midnight. Exogenous corticosteroids suppress adrenocortical activity the least, when given at the time of maximal activity (a.m.).
7. In using alternate-day therapy it is important, as in all therapeutic situations, to individualize and tailor the therapy to each patient. Complete control of symptoms will not be possible in all patients. An explanation of the benefits of alternate-day therapy will help the patient to understand and tolerate the possible flare-up in symptoms which may occur in the latter part of the off-steroid day. Other symptomatic therapy may be added or increased at this time if needed.
8. In the event of an acute flare-up of the disease process, it may be necessary to return to a full suppressive daily divided corticoid dose for control. Once control is again established, alternate-day therapy may be reinstituted.
9. Although many of the undesirable features of corticosteroid therapy can be minimized by alternate-day therapy, as in any therapeutic situation, the physician must carefully weigh the benefit-risk ratio for each patient with whom corticoid therapy is being considered.

HOW SUPPLIED

Prednisolone tablets, USP, 5 mg are scored, round, yellow tablets debossed with "XJ" on the scored side and with "011" on the other side, supplied in:

- bottles of 100 (NDC60722-5011-0)
- bottles of 1000 (NDC60722-5011-1)

Dispense in a well-closed container with child-resistant closure.

Store at 20° to 25°C (68° to 77°F); excursions permitted to 15° to 30°C (59° to 86°F) [See USP Controlled Room Temperature].

Manufactured by:

Zhejiang Xianju Pharmaceutical Co., Ltd. (FDF Site)
Taizhou, Zhejiang, 317300, China

Rev. 02/2024

PACKAGE LABEL.PRINCIPAL DISPLAY PANEL

NDC 60722-5011-0

PrednisoLONE Tablets USP

5 mg

Rx only
100 Tablets

PACKAGE LABEL.PRINCIPAL DISPLAY PANEL

NDC 60722-5011-1

PrednisoLONE Tablets USP

5 mg

Rx only
1000 Tablets